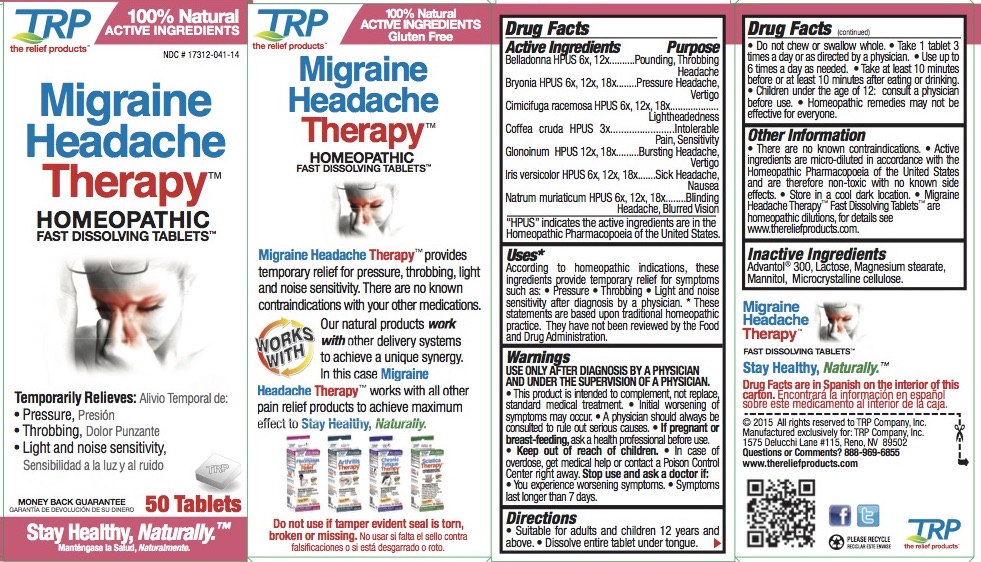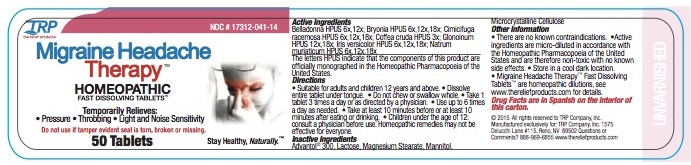 DRUG LABEL: Migraine Headache Therapy
NDC: 17312-041 | Form: TABLET, ORALLY DISINTEGRATING
Manufacturer: TRP Company
Category: homeopathic | Type: HUMAN OTC DRUG LABEL
Date: 20251215

ACTIVE INGREDIENTS: ATROPA BELLADONNA 6 [hp_X]/1 1; BRYONIA ALBA ROOT 6 [hp_X]/1 1; BLACK COHOSH 6 [hp_X]/1 1; ARABICA COFFEE BEAN 3 [hp_X]/1 1; NITROGLYCERIN 12 [hp_X]/1 1; IRIS VERSICOLOR ROOT 6 [hp_X]/1 1; SODIUM CHLORIDE 6 [hp_X]/1 1
INACTIVE INGREDIENTS: SORBITOL; CROSPOVIDONE; CELLULOSE, MICROCRYSTALLINE; COPOVIDONE; SILICON DIOXIDE; LACTOSE; MAGNESIUM STEARATE; MANNITOL

Migraine Headache Therapy™ Homeopathic Fast Dissolving Tablets

Active Ingredients |  | Purpose
Belladonna HPUS | 6x, 12x | Pounding, Throbbing Headache
Bryonia HPUS | 6x, 12x, 18x | Pressure Headache, Vertigo
Cimicifuga racemosa HPUS | 6x, 12x, 18x | Lightheadedness
Coffea cruda | HPUS 3x | Intolerable Pain, Sensitivity
Glonoinum HPUS | 12x, 18x | Bursting Headache, Vertigo
Iris versicolor HPUS | 6x, 12x, 18x | Sick Headache, Nausea
Natrum muriaticum HPUS | 6x, 12x, 18x | Blinding Headache, Blurred Vision

"HPUS" indicates the active ingredients are in the Homeopathic Pharmacopoeia of the United States.

Uses:*
According to homeopathic indications, these ingredients provide temporary relief for symptoms such as: • Pressure • Throbbing • Light and noise sensitivity after diagnosis by a physician.
*These statements are based upon traditional homeopathic practice. They have not been reviewed by the Food and Drug Administration.

Warnings:

USE ONLY AFTER DIAGNOSIS BY A PHYSICIAN AND UNDER THE SUPERVISION OF A PHYSICIAN.

- This product is intended to complement, not replace, standard medical treatment.
- Initial worsening of symptoms may occur.
- A physician should always be consulted to rule out serious causes.

PREGNANCY OR BREAST FEEDING

If pregnant or breast-feeding, ask a health professional before use.

WARNINGS

- In case of overdose, get medical help or contact a Poison Control Center right away.

Stop use and ask a doctor if:

- You experience worsening symptoms.
- If symptoms last longer than 7 days.

Directions

- Suitable for adults and children 12 years and above.
- Dissolve entire tablet under tongue.
- Do not chew or swallow whole.
- Take 1 tablet 3 times a day or as directed by a physician.
- Use up to 6 times a day as needed.
- Take at least 10 minutes before or at least 10 minutes after eating or drinking.
- Children under the age of 12: consult a physician before use.
- May take up to 60 days to see results.
- Homeopathic remedies may not be effective for everyone.

Other information

- There are no known contraindications.
- Active ingredients are micro-diluted in accordance with the Homeopathic Pharmacopoeia of the United States and are therefore non-toxic with no known side effects.
- Store in a cool dark location.
- Migraine Headache Therapy™ Homeopathic Fast Dissolving Tablet are homeopathic dilutions: see www.thereliefproducts.com for details.

Inactive Ingredients

Advantol® 300, Lactose, Magnesium Stearate, Mannitol, Microcrystalline Cellulose.

Questions or comments? www.thereliefproducts.com, 1-888-969-6855